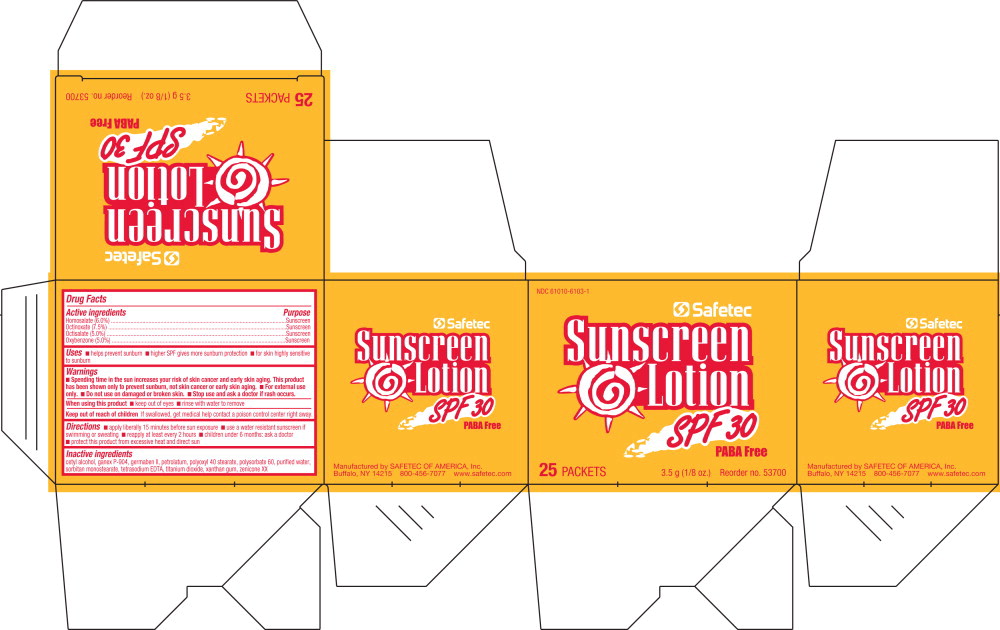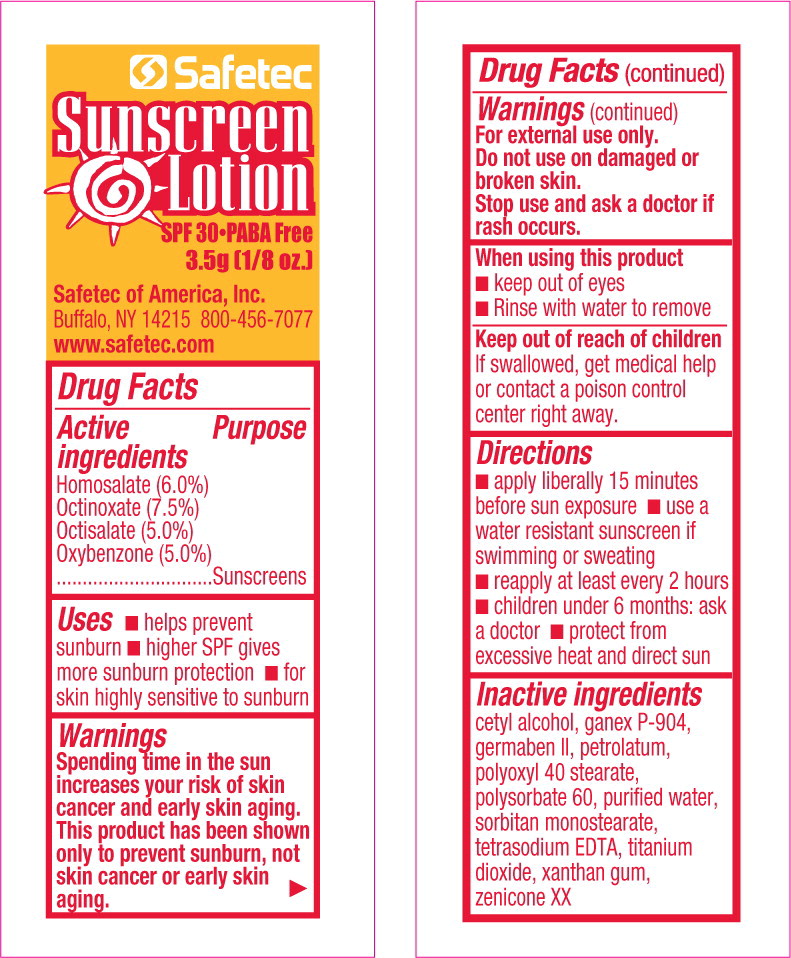 DRUG LABEL: Sunscreen
NDC: 61010-6103 | Form: LOTION
Manufacturer: Safetec of America, Inc.
Category: otc | Type: HUMAN OTC DRUG LABEL
Date: 20240208

ACTIVE INGREDIENTS: HOMOSALATE 6 mg/1 g; OCTINOXATE 7.5 mg/1 g; OCTISALATE 5 mg/1 g; OXYBENZONE 5 mg/1 g
INACTIVE INGREDIENTS: CETYL ALCOHOL; POVIDONE K30; PROPYLENE GLYCOL; PROPYLPARABEN; METHYLPARABEN; DIAZOLIDINYL UREA; POLYOXYL 40 STEARATE; POLYSORBATE 60; PETROLATUM; WATER; SORBITAN MONOSTEARATE; EDETATE SODIUM; TITANIUM DIOXIDE; XANTHAN GUM; POLYETHYLENE GLYCOL 400; DIMETHICONE

61010-6103, Sunscreen

Drug Facts

Active Ingredient

Homosalate (6.0%)

Octinoxate (7.5%)

Octisalate (5.0%)

Oxybenzone (5.0%)

Purpose

Sunscreens

Uses

- helps prevent sunburn
- higher SPF gives more sunburn protection
- for skin highly sensitive to sunburn

Warnings

Spending time in the sun increases your risk of skin cancer and early skin aging. This product has been shown only to prevent sunburn, not skin cancer or early skin aging.

For external use only.

Do not use on damaged or broken skin.

Stop use and ask a doctor if rash occurs.

When using this product

- keep out of eyes
- rinse with water to remove

Keep out of reach of children.

If swallowed, get medical help or contact a poison control center right away

Directions

- apply liberally 15 minutes before sun exposure
- use a water resistant sunscreen if swimming or sweating
- reapply at least every two hours
- children under 6 months: ask a doctor
- protect from excessive heat and direct sun

Inactive ingredients

cetyl alcohol, ganex P-904, germaben II, petrolatum, polyoxyl 40 stearate, polysorbate 60, purified water, sorbitan monostearate, tetrasodium EDTA, titanium dioxide, xanthan gum, zenicone XX

PACKAGE LABEL

PRINCIPAL DISPLAY PANEL – 25 count box

NDC 61010-6103-1

Safetec

Sunscreen
Lotion
SPF 30

PABA Free

25 Packets

3.5 g (1/8 oz.)

Reorder no. 53700

PACKAGE LABEL

PRINCIPAL DISPLAY PANEL – packet

Safetec

Sunscreen
Lotion
SPF 30•PABA Free
3.5g (1/8 oz.)

Safetec of America, Inc.
Buffalo, NY 14215 800-456-7077
www.safetec.com